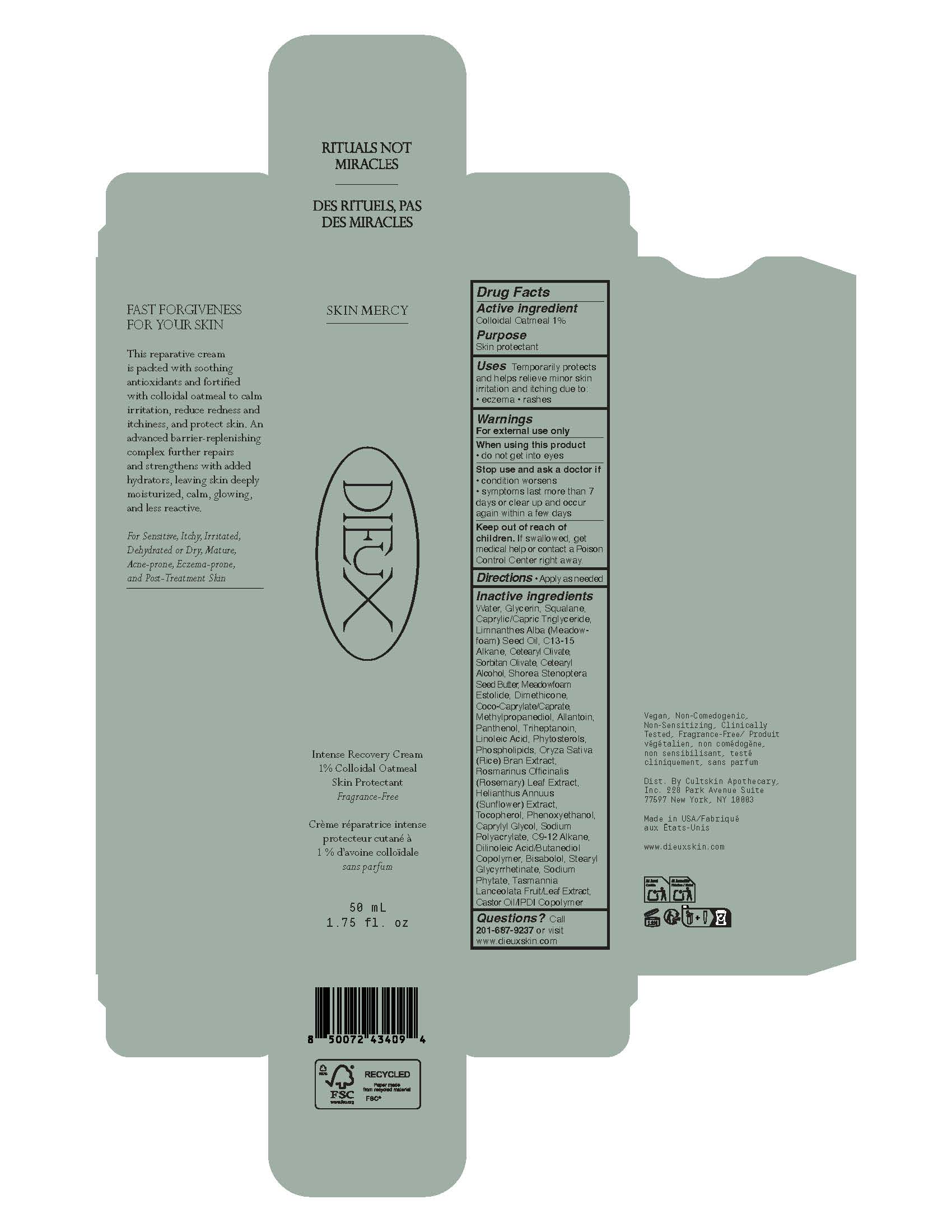 DRUG LABEL: Skin Mercy Intense Recovery Cream
NDC: 80921-001 | Form: CREAM
Manufacturer: Cultskin Apothecary, Inc.
Category: otc | Type: HUMAN OTC DRUG LABEL
Date: 20260225

ACTIVE INGREDIENTS: OATMEAL 1 g/100 mL
INACTIVE INGREDIENTS: CAPRYLYL GLYCOL; C9-12 ALKANE; ROSEMARY; CASTOR OIL/IPDI COPOLYMER; SORBITAN OLIVATE; CETEARYL OLIVATE; COCO-CAPRYLATE/CAPRATE; TRIHEPTANOIN; TOCOPHEROL; SODIUM PHYTATE; CAPRYLIC/CAPRIC TRIGLYCERIDE; ALLANTOIN; DIMETHICONE; METHYLPROPANEDIOL; LINOLEIC ACID; ORYZA SATIVA (RICE) BRAN; SODIUM POLYACRYLATE (2500000 MW); TASMANNIA LANCEOLATA WHOLE; PANTHENOL; GLYCERIN; PHENOXYETHANOL; WATER; C13-15 ALKANE; BISABOLOL; SQUALANE; SHOREA STENOPTERA SEED BUTTER; MEADOWFOAM ESTOLIDE; MEADOWFOAM SEED OIL; CETEARYL ALCOHOL; HELIANTHUS ANNUUS FLOWERING TOP; STEARYL GLYCYRRHETINATE; DILINOLEIC ACID/BUTANEDIOL COPOLYMER

Drug Facts

Active ingredient

Colloidal Oatmeal 1%

Purpose

Skin protectant

Uses

Temporarily protects and helps relieve minor skin irritation and itching due to:

- eczema
- rashes

Warnings

For external use only

When using this product

- do not get into eyes

Stop use and ask a doctor if

- condition worsens
- symptoms last more than 7 days or clear up and occur again within a few days

Keep out of reach of children. If swallowed, get medical help or contact a Poison Control Center right away.

Directions

- Apply as needed

Inactive ingredients

Water, Glycerin, Squalane, Caprylic/Capric Triglyceride, Limnanthes Alba (Meadowfoam) Seed Oil, C13-15 Alkane, Cetearyl Olivate, Sorbitan Olivate, Cetearyl Alcohol, Shorea Stenoptera Seed Butter, Meadowfoam Estolide, Dimethicone, Coco-Caprylate/Caprate, Methylpropanediol, Allantoin, Panthenol, Triheptanoin, Linoleic Acid, Phytosterols, Phospholipids, Oryza Sativa (Rice) Bran Extract, Rosmarinus Officinalis (Rosemary) Leaf Extract, Helianthus Annuus (Sunflower) Extract, Tocopherol, Phenoxyethanol, Caprylyl Glycol, Sodium Polyacrylate, C9-12 Alkane, Dilinoleic Acid/Butanediol Copolymer, Bisabolol, Stearyl Glycyrrhetinate, Sodium Phytate, Tasmannia Lanceolata Fruit/Leaf Extract, Castor Oil/IPDI Copolymer

Questions?

Call 201-687-9237 or visit www.dieuxskin.com

Principal Display Panel - 50 mL Tube

SKIN MERCY

DIEUX

Intense Recovery Cream
1% Colloidal Oatmeeal
Skin Protectant
Fragrance-Free

Crème réparatrice intense
protecteur cutané à
1% d’avoine colloïdale
sans parfum

50 mL
1.75 fl. oz